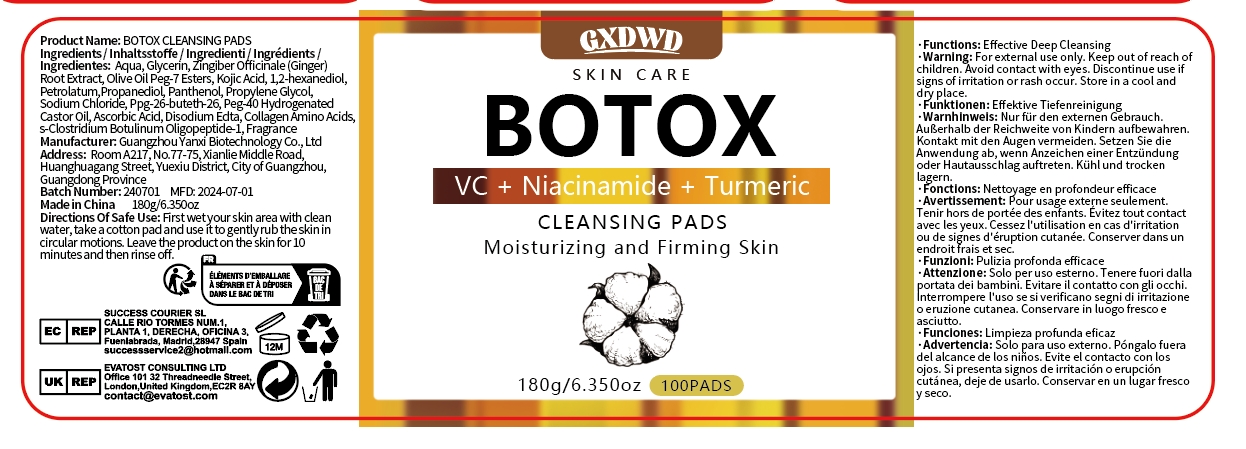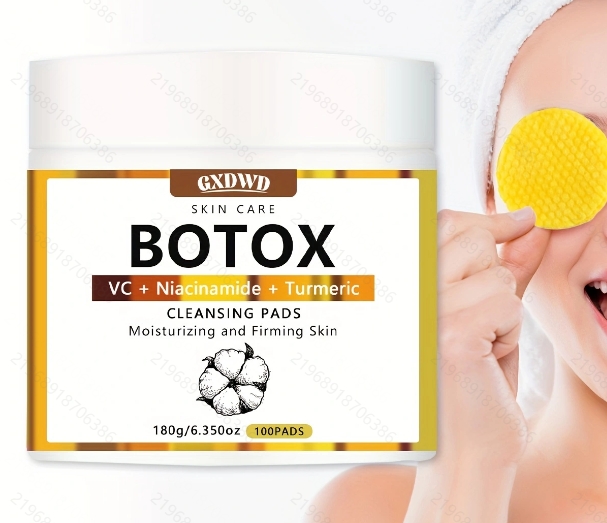 DRUG LABEL: CLEANSING PADS
NDC: 84025-273 | Form: FILM
Manufacturer: Guangzhou Yanxi Biotechnology Co., Ltd
Category: otc | Type: HUMAN OTC DRUG LABEL
Date: 20241126

ACTIVE INGREDIENTS: GLYCERIN 5 mg/100 g; ZINGIBER OFFICINALE (GINGER) ROOT EXTRACT 3 mg/100 g
INACTIVE INGREDIENTS: WATER

DOSAGE AND ADMINISTRATION

First wet your skin area with clean water, take a cotton pad and use it to gently rub the skin in circular motions. Leave the product on the skin for10 minutes and then rinse off.

WARNINGS

keep out of children

INACTIVE INGREDIENT

Aqua

INDICATIONS AND USAGE

For daily face care

keep out of children

PURPOSE

Brightens & Energizes SkinEnhances Skin's Natural Glow
lmproves Overall Texture